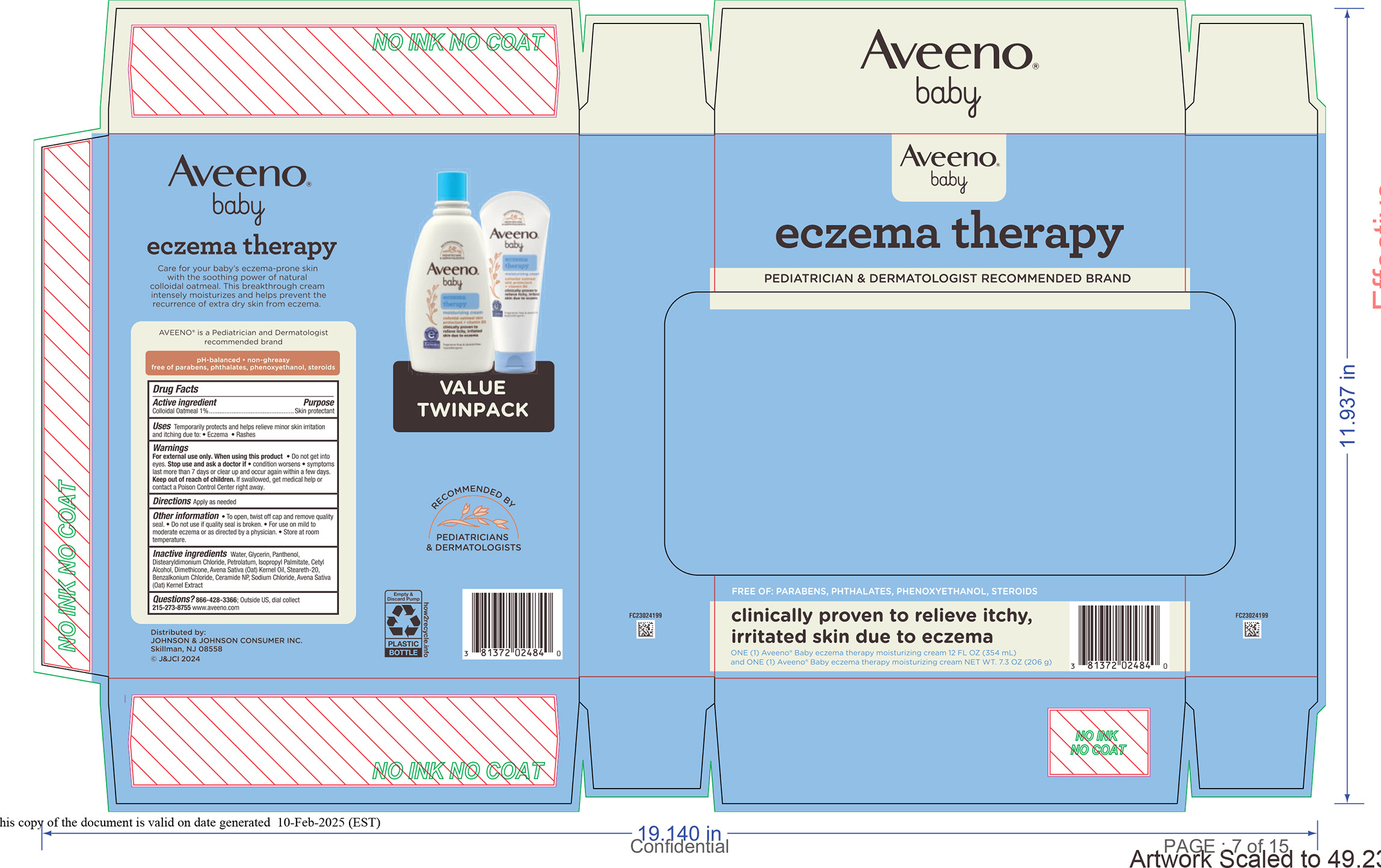 DRUG LABEL: Aveeno Baby Eczema Therapy Moisturizing Cream Clubtray
NDC: 69968-0921 | Form: KIT | Route: TOPICAL
Manufacturer: Kenvue Brands LLC
Category: otc | Type: HUMAN OTC DRUG LABEL
Date: 20250213

ACTIVE INGREDIENTS: OATMEAL 10 mg/1 mL; OATMEAL 10 mg/1 g
INACTIVE INGREDIENTS: STEARETH-20; GLYCERIN; PANTHENOL; DISTEARYLDIMONIUM CHLORIDE; DIMETHICONE; WATER; CETYL ALCOHOL; PETROLATUM; AVENA SATIVA (OAT) KERNEL OIL; OAT; BENZALKONIUM CHLORIDE; CERAMIDE NP; SODIUM CHLORIDE; ISOPROPYL PALMITATE; STEARETH-20; GLYCERIN; PANTHENOL; DISTEARYLDIMONIUM CHLORIDE; DIMETHICONE; WATER; CETYL ALCOHOL; PETROLATUM; AVENA SATIVA (OAT) KERNEL OIL; OAT; BENZALKONIUM CHLORIDE; CERAMIDE NP; SODIUM CHLORIDE; ISOPROPYL PALMITATE

Aveeno Baby Eczema Therapy Moisturizing Cream Clubtray

Aveeno Baby Eczema Therapy Moisturizing Cream Clubtray

Drug Facts

Active ingredients

Colloidal Oatmeal 1%

Purpose

Skin protectant

Uses

Temporarily protects and helps relieve minor skin irritation and itching due to:

• Eczema • Rashes

Warnings

For external use only

When using this product • Do not get into eyes.

Stop use and ask a doctor if • condition worsens • symptoms last more than 7 days or clear up and occur again within a few days.

Keep out of reach of children. If swallowed, get medical help or contact a Poison Control Center right away.

Directions

Apply as needed

Other information

• To open, twist off cap and remove quality seal. • Do not use if quality seal is broken. • For use on mild to moderate eczema or as directed by a physician. • Store at room temperature.

Inactive ingredients

Water, Glycerin, Panthenol, Distearyldimonium Chloride, Petrolatum, Isopropyl Palmitate, Cetyl Alcohol, Dimethicone, Avena Sativa (Oat) Kernel Oil, Steareth-20, Benzalkonium Chloride, Ceramide NP, Sodium Chloride, Avena Sativa (Oat) Kernel Extract

Questions?

866-428-3366; Outside US, dial collect 215-273-8755 www.aveeno.com

Distributed by:
JOHNSON & JOHNSON CONSUMER INC.
Skillman, NJ 08558

PRINCIPAL DISPLAY PANEL - Kit Package

Aveeno ®

baby

eczema therapy

PEDIATRICIAN & DERMATOLOGIST RECOMMENDED BRAND

FREE OF: PARABENS, PHTHALATES, PHENOXYETHANOL, STEROIDS

clinically proven to relieve itchy,

irritated skin due to eczema

ONE (1) Aveeno® Baby eczema therapy moisturizing cream 12 FL OZ (354 mL)

and ONE (1) Aveeno® Baby eczema therapy moisturizing cream NET WT. 7.3 OZ (206 g)